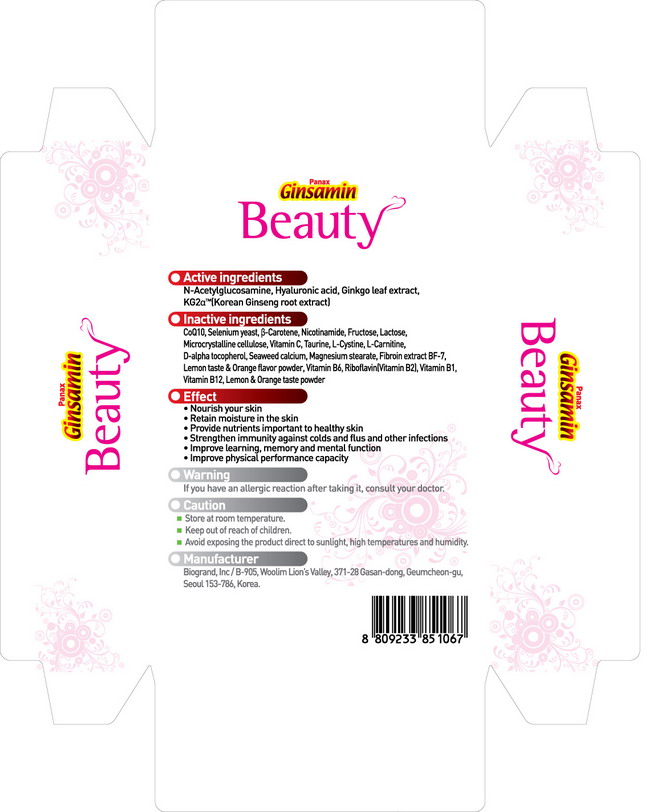 DRUG LABEL: Ginsamin Beauty
NDC: 44738-6001 | Form: GRANULE
Manufacturer: Biogrand Co., Ltd
Category: otc | Type: HUMAN OTC DRUG LABEL
Date: 20100307

ACTIVE INGREDIENTS: GINKGO 150 mg/2000 mg; ASIAN GINSENG 150 mg/2000 mg; N-ACETYLGLUCOSAMINE 200 mg/2000 mg; HYALURONIC ACID 60 mg/2000 mg

Drug Facts

Active Ingredient: Ginkgo leaf extract, Korean ginseng root extract, N-Acetylglucosamine, L-Cystine, Hyaluronic acid

DESCRIPTION

Product name
Panax Ginsamin Beauty
Active ingredients
Ginkgo leaf extract, Korean ginseng root extract, N-Acetylglucosamine, Hyaluronic acid
Inactive ingredients
taurine, lactose, microcrystalline cellulose, D-alpha tocopherol, vitamin B1, riboflavin,
vitamin B6, vitamin B12, L-cystine, vitamin C, lemon juice, orange juice, selenium yeast,
B-carotene, L-carnitine, fructose, magnesium stearate
Effect
• improve learning, memory and mental function
• improve learning and memory, cognitive function and concentration
• improve physical performance capacity
• strengthen immunity against colds and flus and other infections
• nourish your skin
• retain moisture in the skin
Warning
If you have an allergic reaction after taking it, consult your doctor
Caution
• Store at room temperature.
• Keep out of reach of children.
• Avoid exposing the product direct to sunlight, high temperatures and humidity.
• Manufacturer
Manufacturer
Biogrand, lnc / B-905, Woolim Lion’s Valley, 371-28 Gasan-dong, Geumcheon-gu, Seoul 153-786, Korea